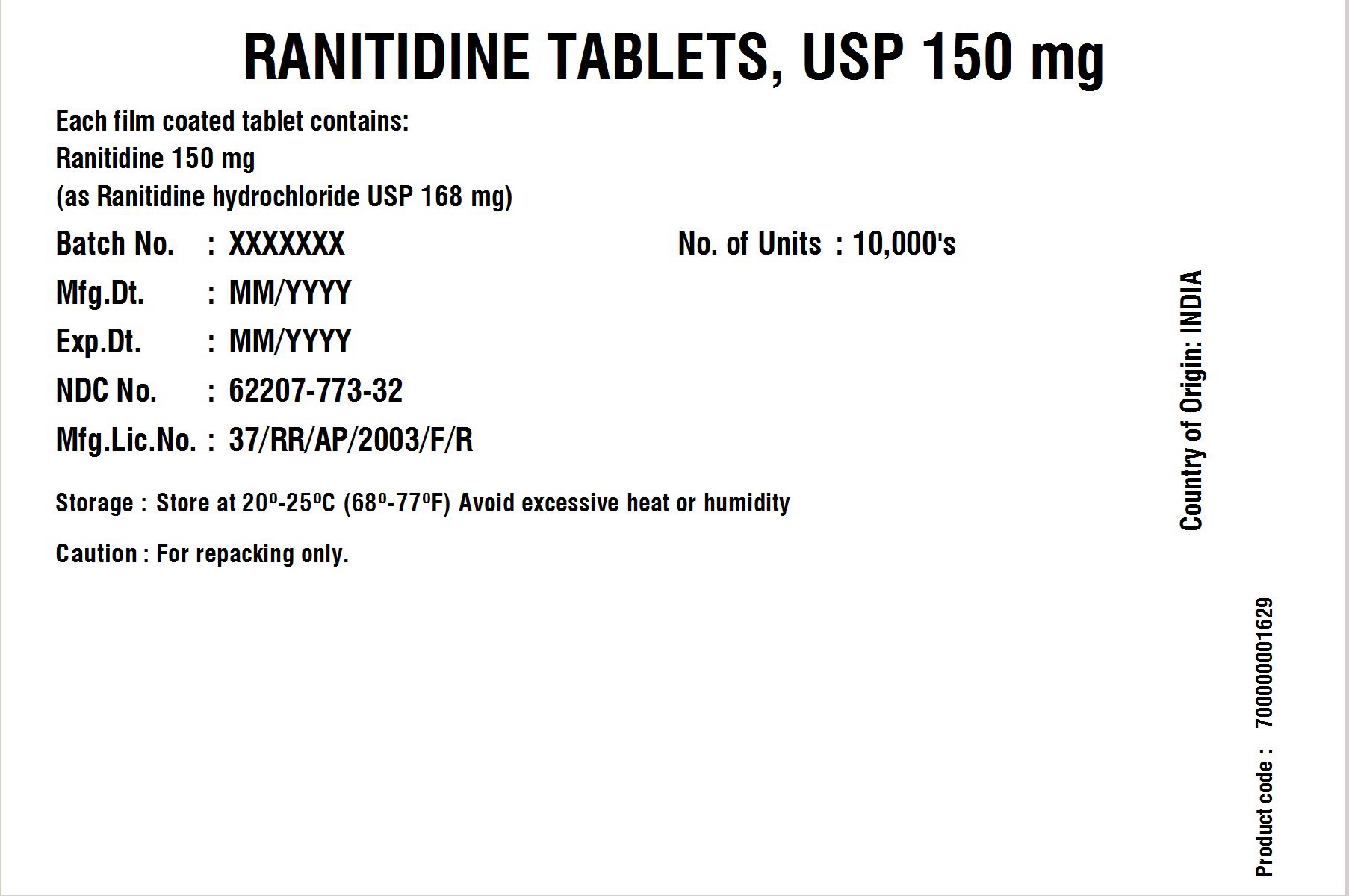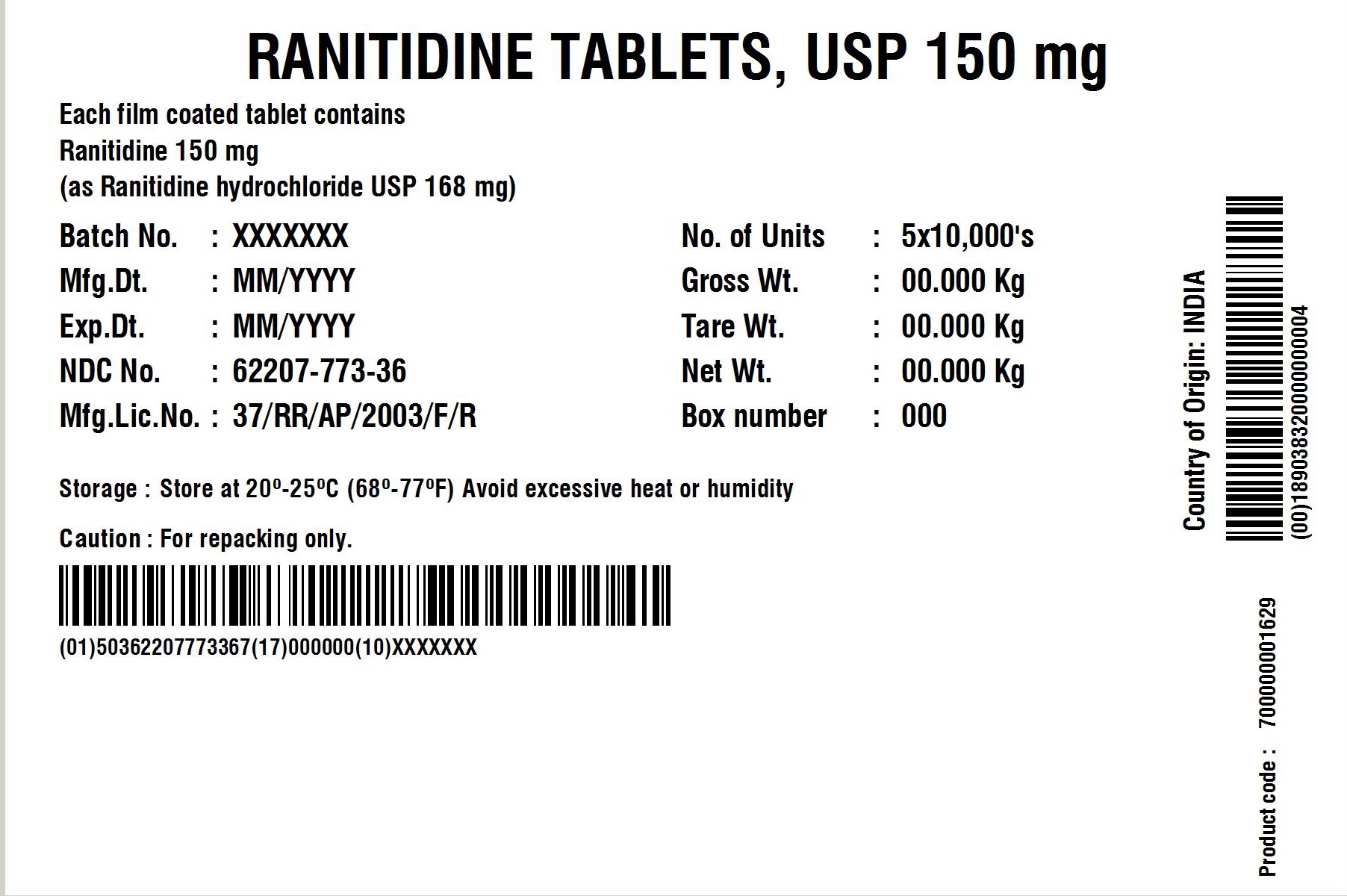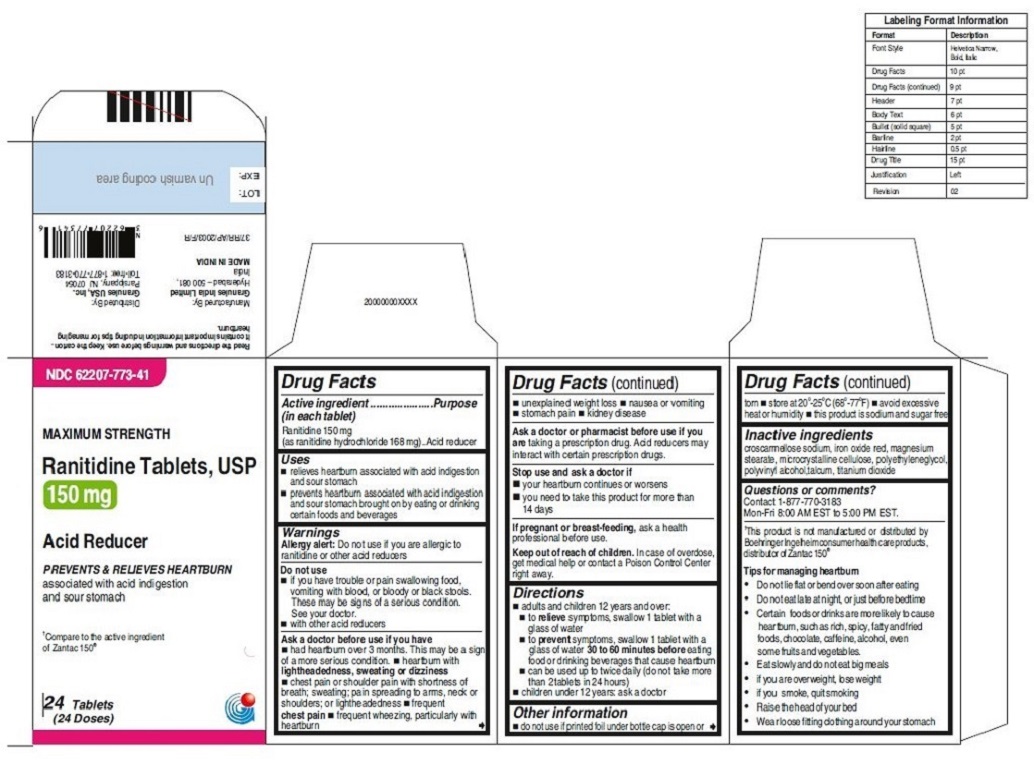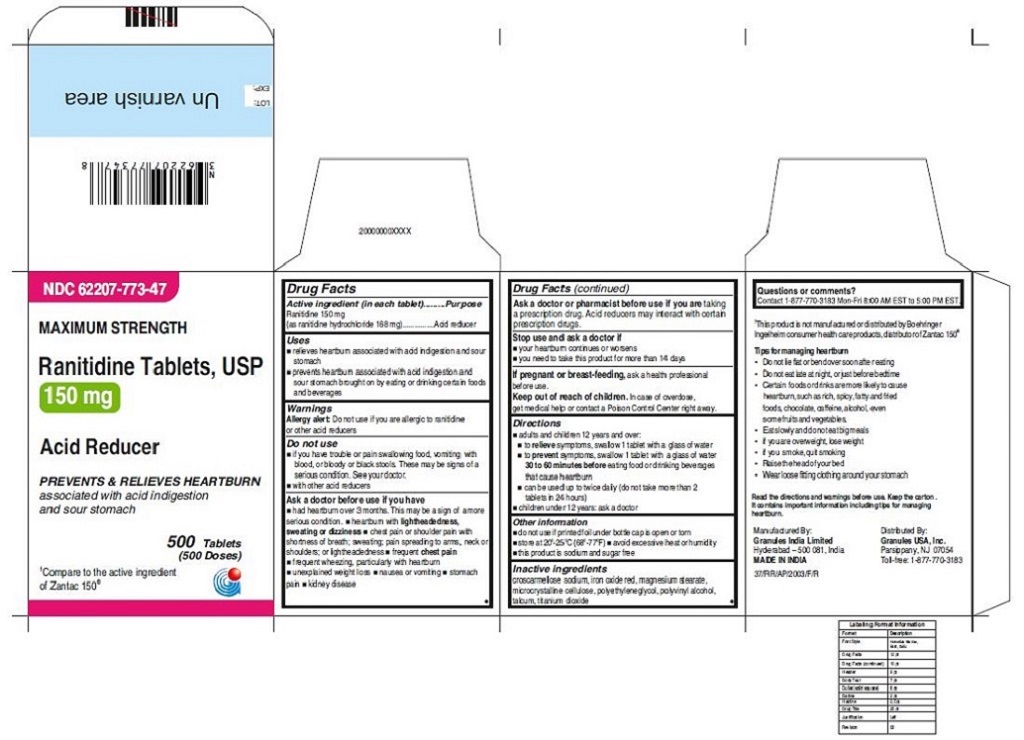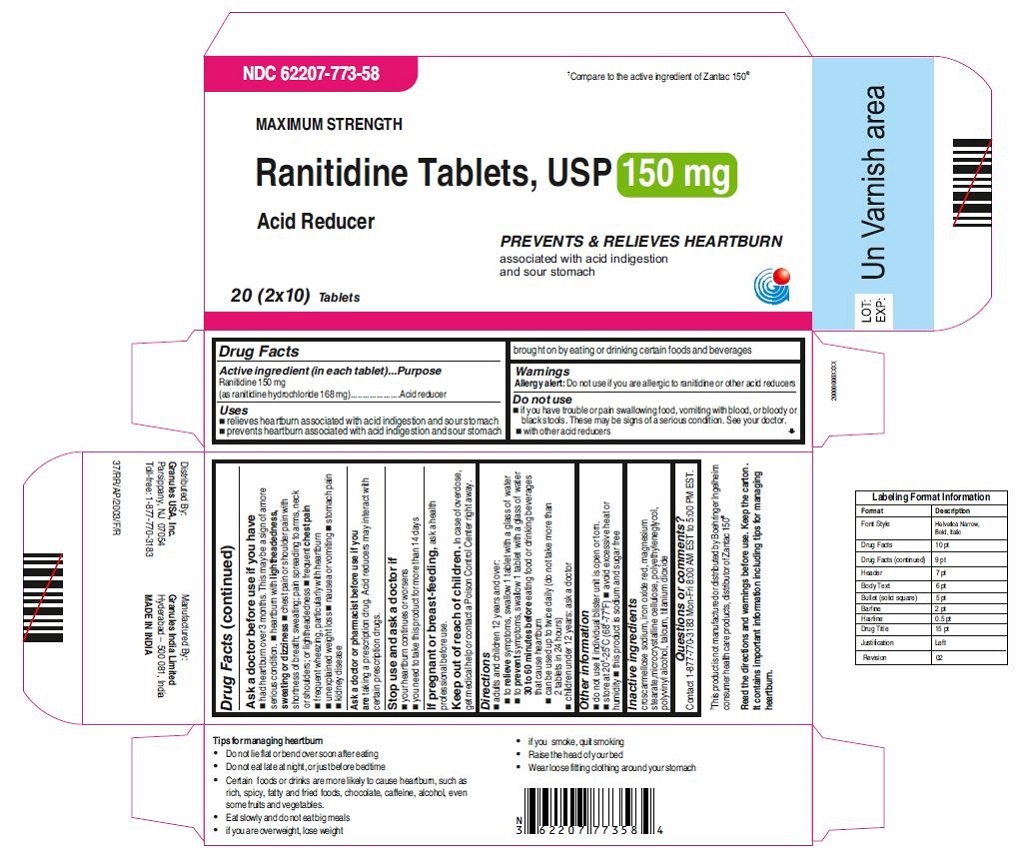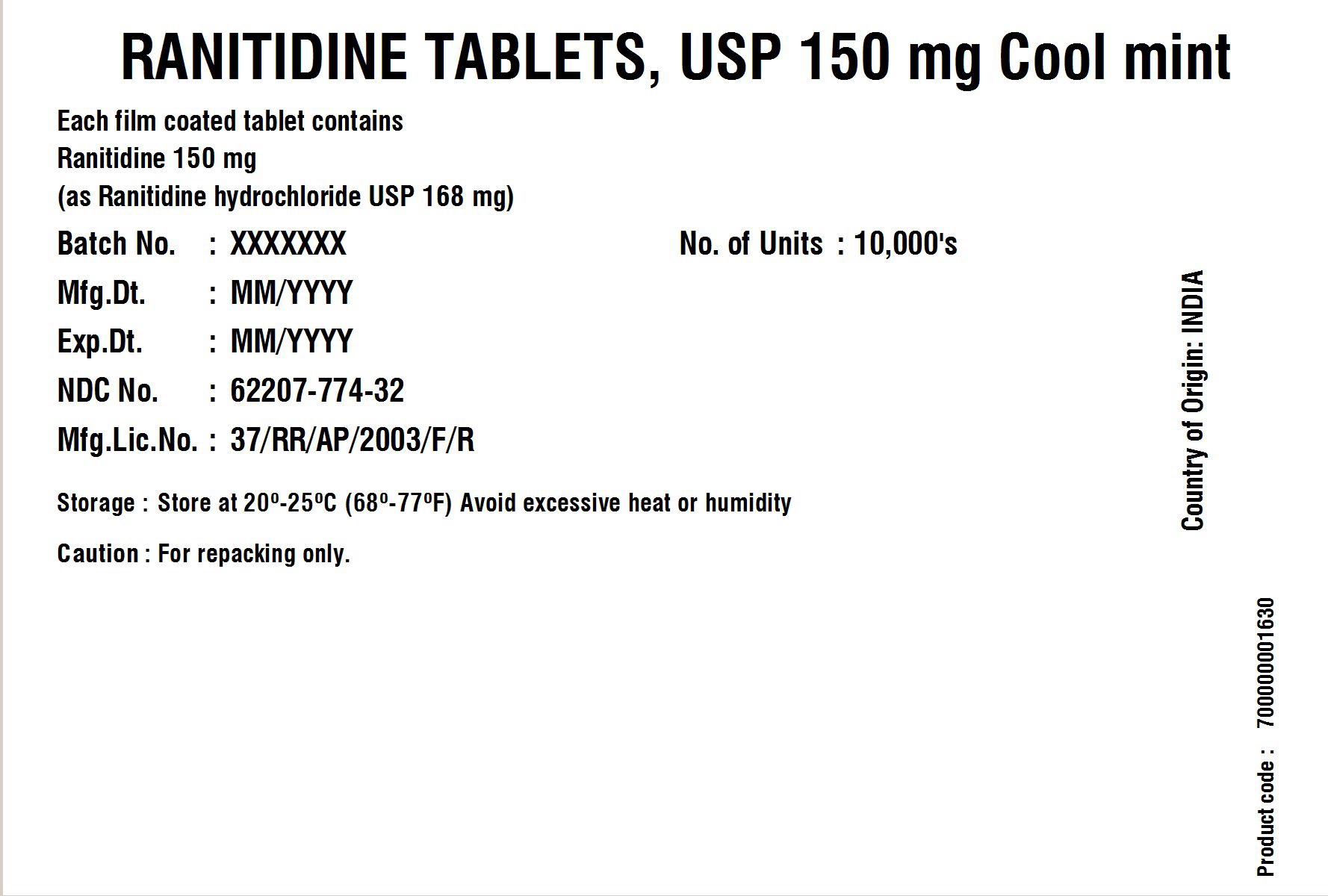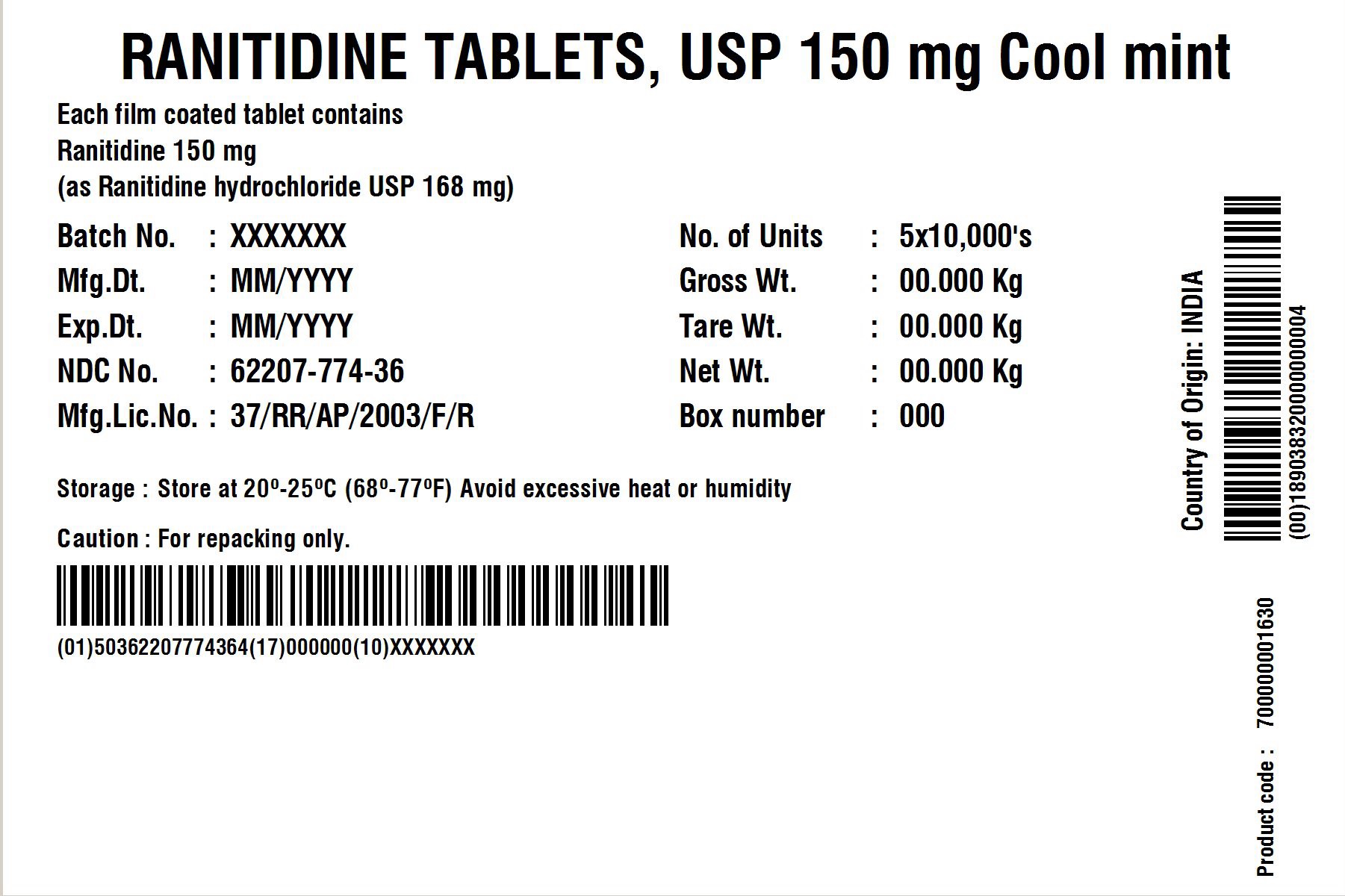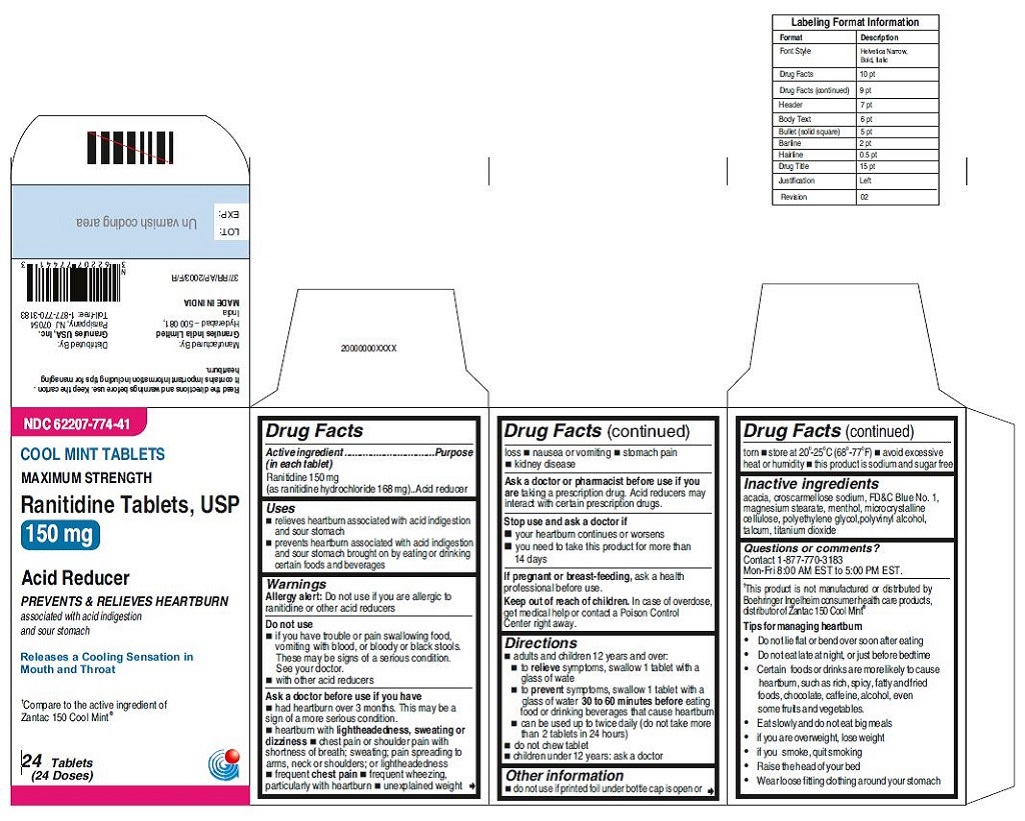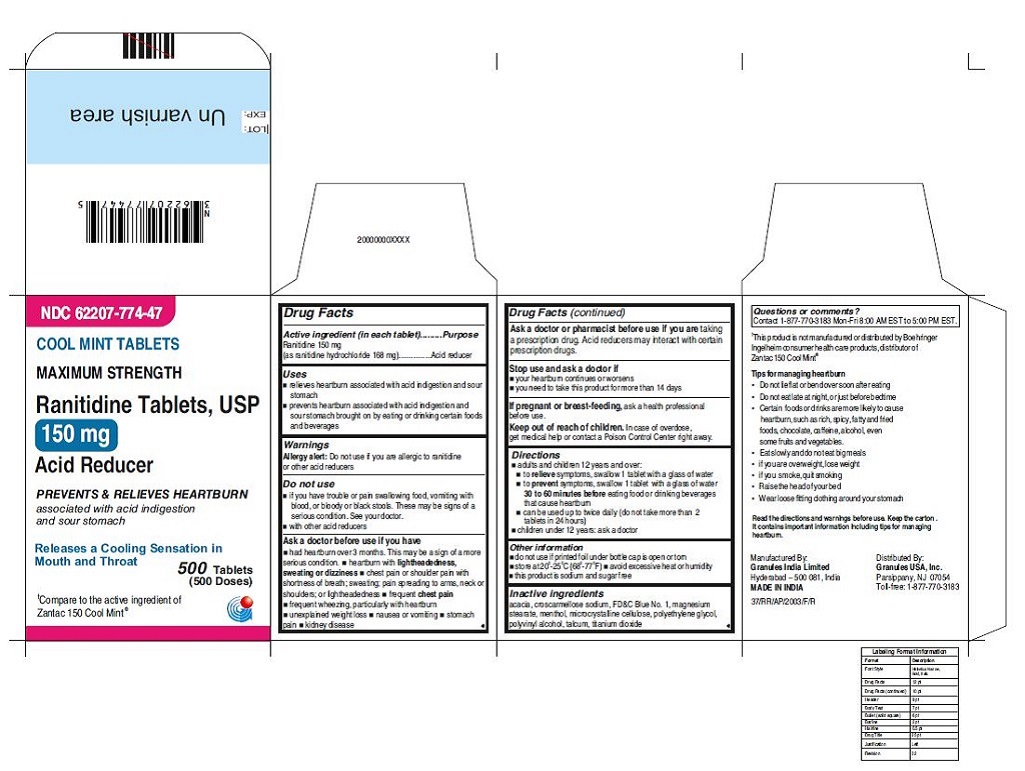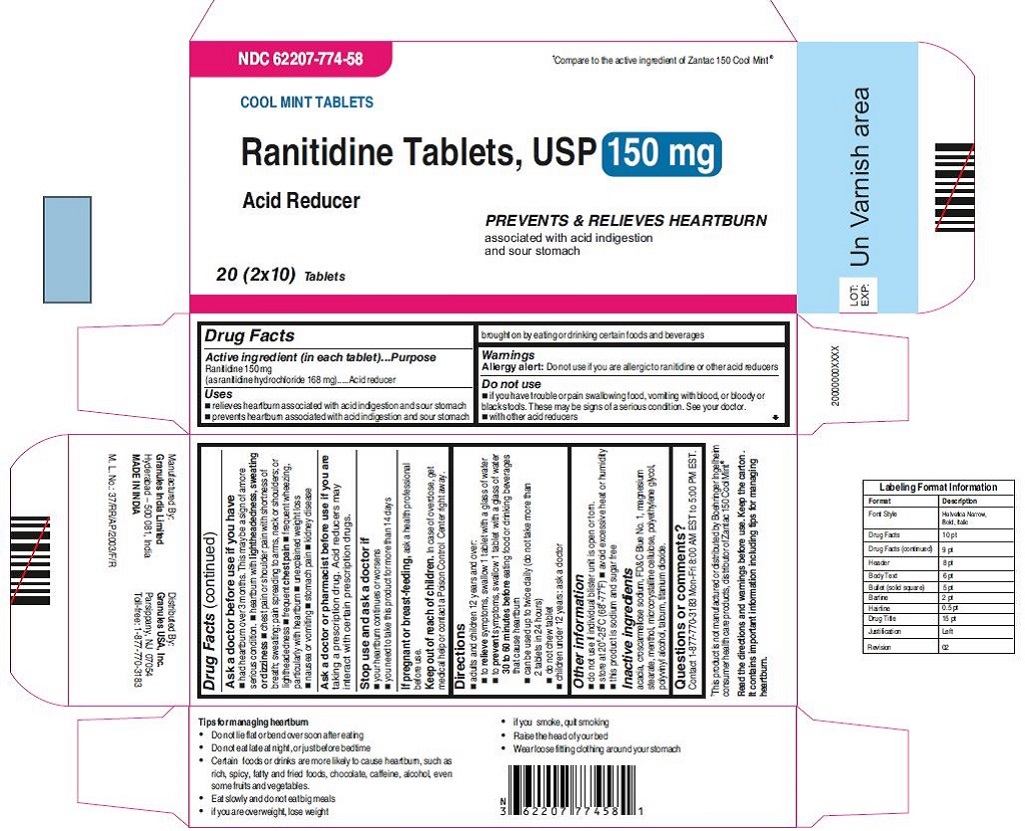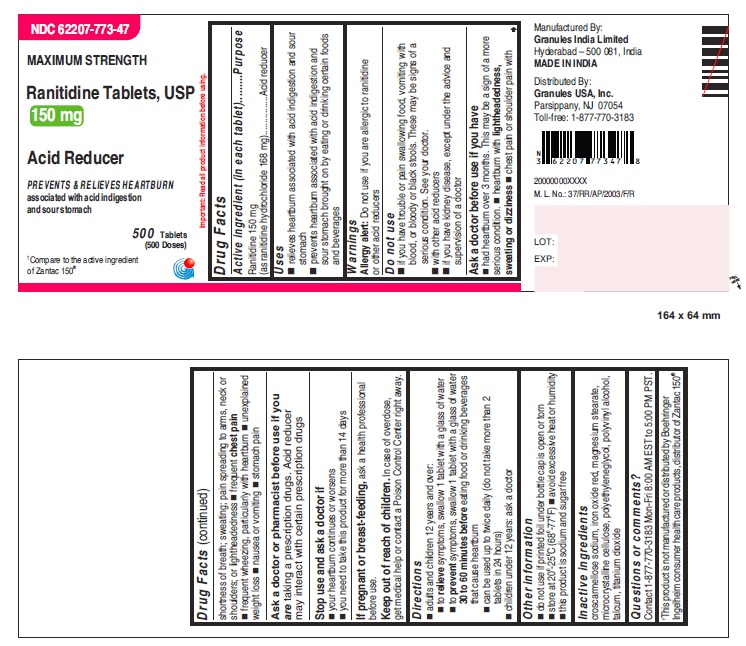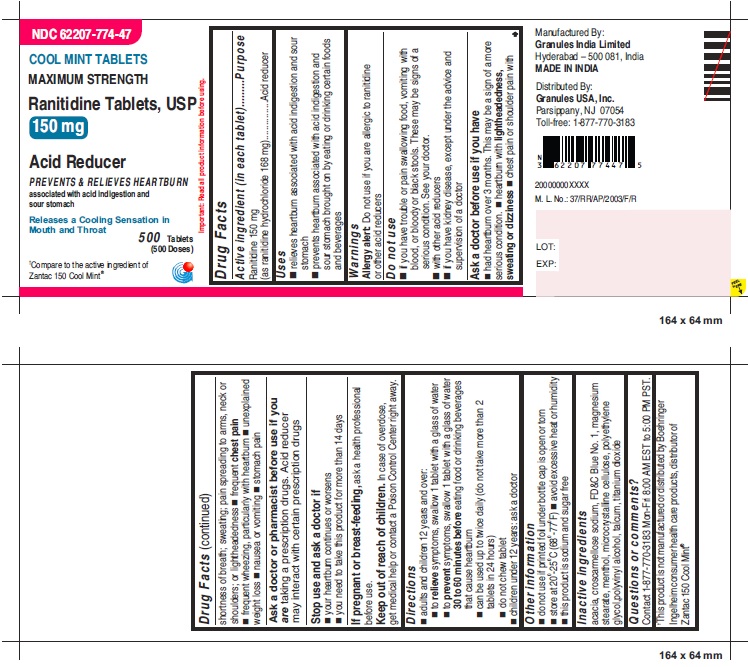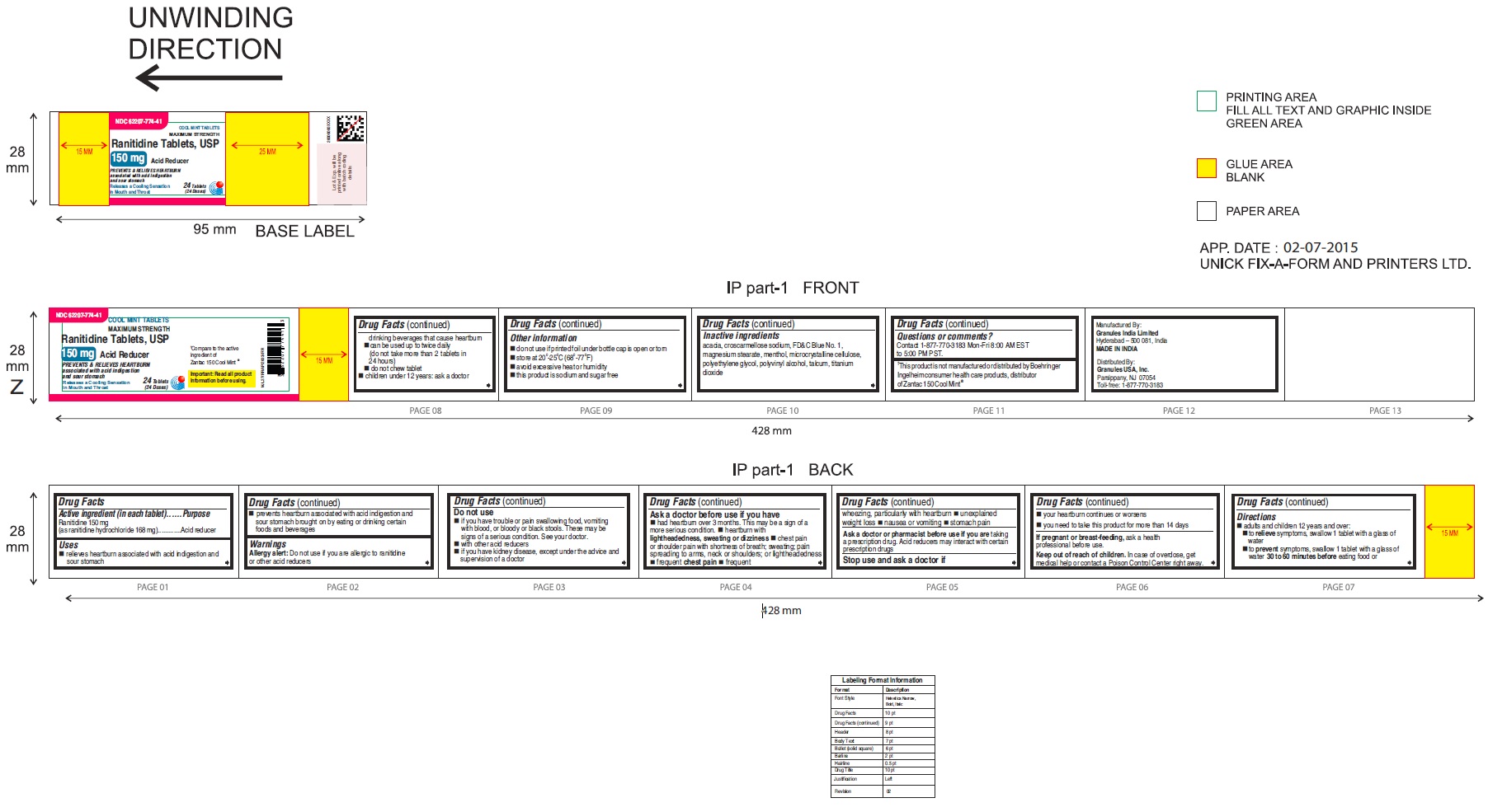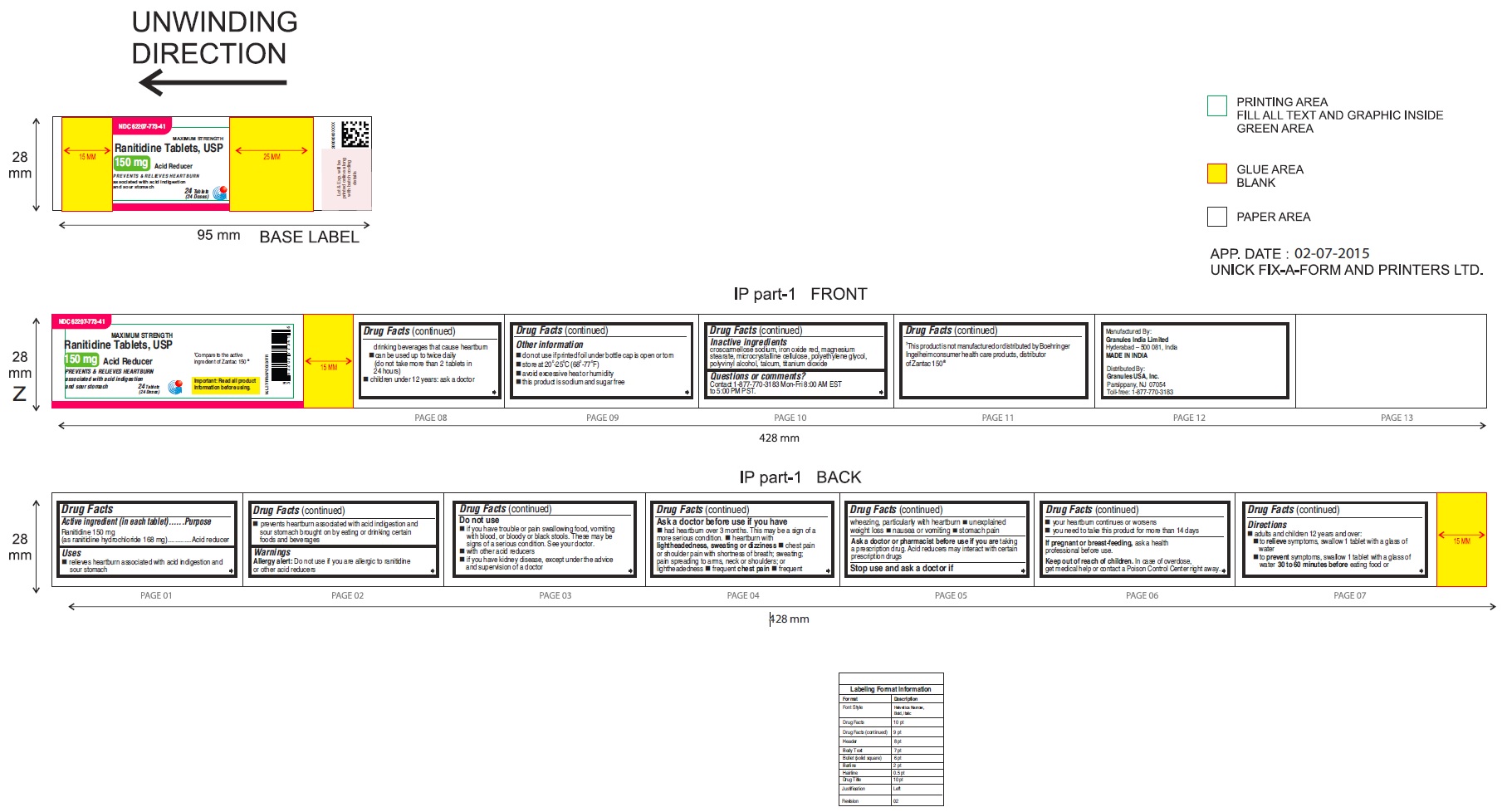 DRUG LABEL: Ranitidine
NDC: 62207-774 | Form: TABLET
Manufacturer: Granules India Ltd
Category: otc | Type: HUMAN OTC DRUG LABEL
Date: 20251202

ACTIVE INGREDIENTS: RANITIDINE HYDROCHLORIDE 150 mg/1 1
INACTIVE INGREDIENTS: ACACIA; CELLULOSE, MICROCRYSTALLINE; CROSCARMELLOSE SODIUM; FD&C BLUE NO. 1; MAGNESIUM STEARATE; MENTHOL; POLYETHYLENE GLYCOL; POLYVINYL ALCOHOL; TALC; TITANIUM DIOXIDE

Ranitidine Tablets

ACTIVE INGREDIENT(S)

Ranitidine 150 mg

PURPOSE

Acid reducer

USE(S)

◾ relieves heartburn associated with acid indigestion and sour stomach
◾ prevents heartburn associated with acid indigestion and sour stomach brought on by eating or
drinking certain foods and beverages

WARNINGS

Allergy alert: Do not use if you are allergic to ranitidine or other acid reducers

DO NOT USE

◾ if you have trouble or pain swallowing food, vomiting with blood, or bloody or black stools. These may be signs of a serious condition. See your doctor.
◾ with other acid reducers

ASK A DOCTOR BEFORE USE IF

◾ had heartburn over 3 months. This may be a sign of a more serious condition.
◾ heartburn with lightheadedness, sweating or dizziness
◾ chest pain or shoulder pain with shortness of breath; sweating; pain spreading to arms, neck or shoulders; or lightheadedness
◾ frequent chest pain
◾ frequent wheezing, particularly with heartburn
◾ unexplained weight loss
◾ nausea or vomiting
◾ stomach pain

◾ kidney disease

Ask a doctor or pharmacist before use if you are taking a prescription drug. Acid reducers may interact with certain prescription drugs.

STOP USE AND ASK DOCTOR IF

◾ your heartburn continues or worsens
◾ you need to take this product for more than 14 days

PREGNANCY/BREASTFEEDING

ask a health professional before use.

KEEP OUT OF REACH OF CHILDREN

In case of overdose, get medical help or contact a Poison Control Center right away.

DIRECTIONS

◾ adults and children 12 years and over:
◾ to relieve symptoms, swallow 1 tablet with a glass of water
◾ to prevent symptoms, swallow 1 tablet with a glass of water

◾ 30 to 60 minutes before eating food or drinking beverages that cause heartburn
◾ can be used up to twice daily (do not take more than 2 tablets in 24 hours)
◾ do not chew tablet (for cool mint tablets only)
◾ children under 12 years: ask a doctor

OTHER INFORMATION

◾ do not use if individual blister unit is open or torn.

◾ do not use if printed foil under bottle cap is open or torn
◾ store at 20^0-25^0C (68^0-77^0F)

◾ avoid excessive heat or humidity
◾ this product is sodium and sugar free

INACTIVE INGREDIENTS

For 150 mg:croscarmellose sodium, iron oxide red, magnesium stearate, microcrystalline cellulose, polyethylene glycol, polyvinyl alcohol,talcum, titanium dioxide
For 150 mg cool mint:acacia, croscarmellose sodium, FD&C Blue No. 1,magnesium stearate, menthol, microcrystalline cellulose,polyethylene glycol, polyvinyl alcohol, talcum,
titanium dioxide

Questions or comments?

•Contact 1-877-770-3183 Mon-Fri 8:00 AM EST to 5:00 PM EST.

This product is not manufactured or distributed by Boehringer Ingelheim ® consumer health care products, distributor of Zantac 150mg and 150mg Cool Mint

Read the directions and warnings before use.

Keep the carton. It contains important information including tips for managing heartburn.

Tips for managing heartburn

•Do not lie flat or bend over soon after eating

•Do not eat late at night, or just before bedtime

•Certain foods or drinks are more likely to cause heartburn, such as rich, spicy, fatty andfried foods, chocolate, caffeine, alcohol, even some fruits and vegetables.

•Eat slowly and do not eat big meals

•if you are overweight, lose weight

•if you smoke, quit smoking

•Raise the head of your bed

•Wear loose fitting clothing around your stomach